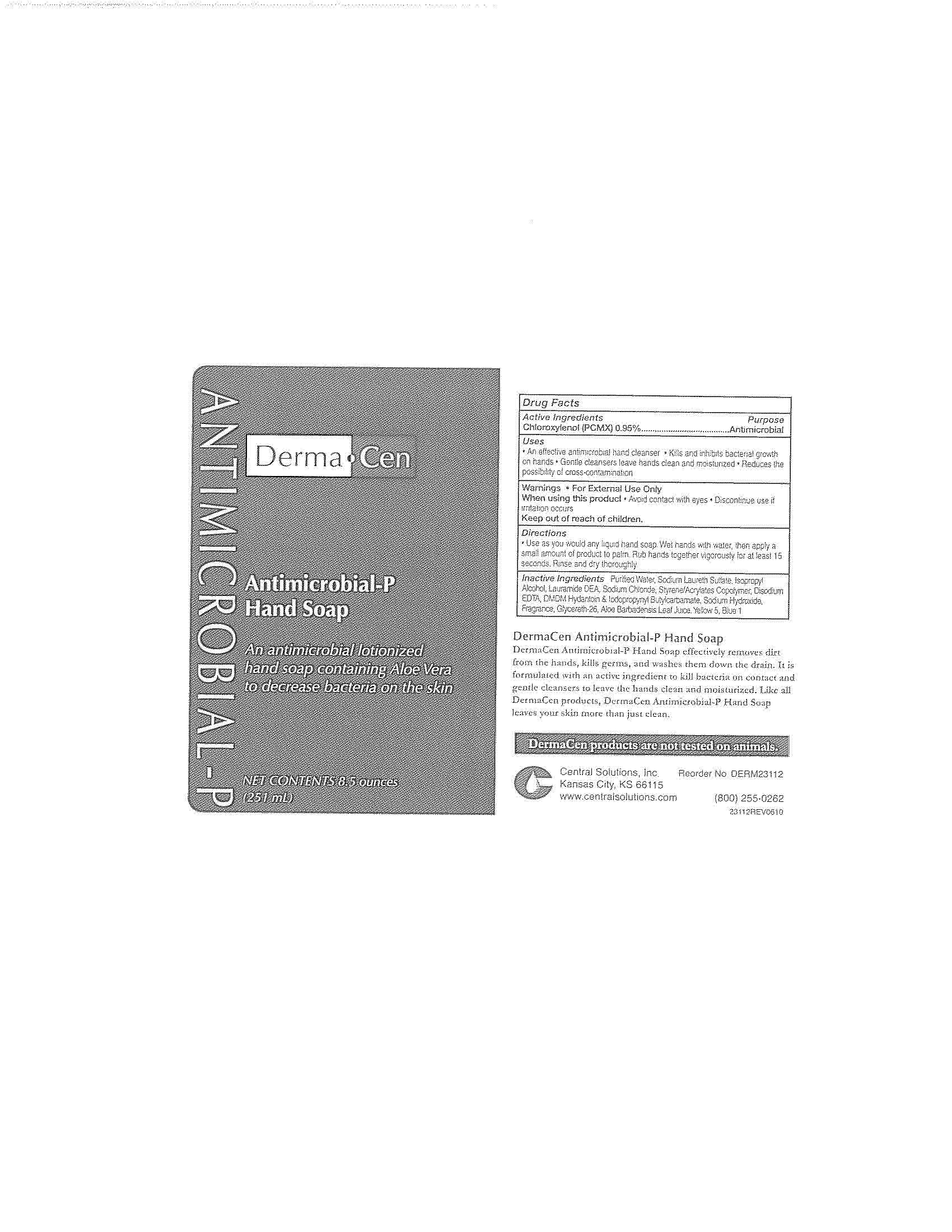 DRUG LABEL: DermaCen Antimicrobial-P Hand
NDC: 62654-231 | Form: LIQUID
Manufacturer: Central Solutions Inc
Category: otc | Type: HUMAN OTC DRUG LABEL
Date: 20241209

ACTIVE INGREDIENTS: CHLOROXYLENOL 0.95 g/100 mL
INACTIVE INGREDIENTS: WATER; SODIUM LAURETH SULFATE; ISOPROPYL ALCOHOL; LAURIC DIETHANOLAMIDE; SODIUM CHLORIDE; EDETATE DISODIUM; DMDM HYDANTOIN; IODOPROPYNYL BUTYLCARBAMATE; SODIUM HYDROXIDE; GLYCERETH-26; ALOE VERA LEAF; FD&C YELLOW NO. 5; FD&C BLUE NO. 1

Drug Facts 62654-231

Active Ingredients

Chloroxylenol (PCMX) 0.95%

Purpose

Antimicrobial

Uses

An effective antimicrobial hand cleanser

Kills and inhibits bacterial growth on hands

Gentle cleansers leave hands clean and moisturized

Reduces the possibility of cross contamination

Warnings

For External Use Only

When using this product

Avoid contact with eyes

Discontinue use if irritation occurs

Keep out of reach of children.

Directions

Use as you would any liquid hand soap.

Wet hands with water, then apply a small amount of product to palm.

Rub hands together vigorously for at least 15 seconds.

Rinse and dry thoroughly.

Inactive Ingredients

Purified Water, Sodium Laureth Sulfate, Isopropyl Alcohol, Lauramide DEA, Sodium Chloride, Styrene/Acrylates Copolymer, Disodium EDTA, DMDM Hydantoin and Iodopropynyl Butylcarbamate, Sodium Hydroxide, Fragrance, Glycereth-26, Aloe Barbadensis Leaf Juice, Yellow 5, Blue 1

PACKAGE LABEL

DermaCen

Antimicrobial-P

Hand Soap

An antimicrobial lotionized

hand soap containing Aloe Vera

to decrease bacteria on the skin

NET CONTENTS 8.5 ounces (251 mL)